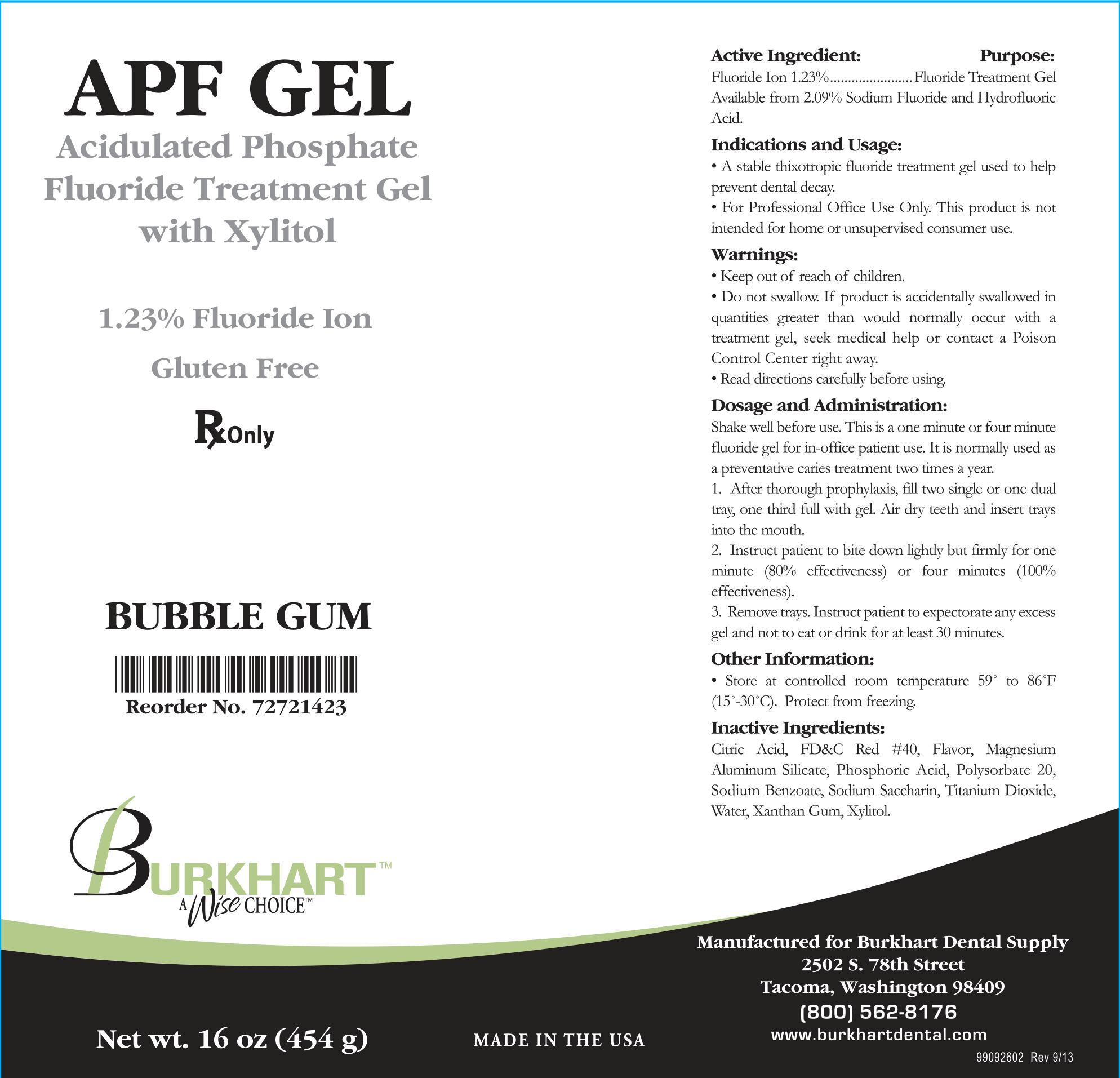 DRUG LABEL: Burkhart
NDC: 43498-103 | Form: GEL
Manufacturer: Burkhart Dental Supply Inc
Category: prescription | Type: HUMAN PRESCRIPTION DRUG LABEL
Date: 20220202

ACTIVE INGREDIENTS: SODIUM FLUORIDE 5.6 g/454 g
INACTIVE INGREDIENTS: CITRIC ACID MONOHYDRATE; MAGNESIUM ALUMINUM SILICATE; PHOSPHORIC ACID; POLYSORBATE 20; SODIUM BENZOATE; SACCHARIN SODIUM; WATER; XANTHAN GUM; XYLITOL; TITANIUM DIOXIDE; FD&C RED NO. 40

Active Ingredient:

Fluoride Ion 1.23%

Available from 2.09% Sodium Fluoride and Hydrofluoric Acid

Purpose:

Fluoride Treatment Gel

Indications and Usage:

- A stable thixotropic fluoride treatment gel used to help prevent dental decay.
- For Professional Use Only. This product is not intended for home or unsupervised use.

Warnings:

- Keep out of reach of children.
- Do not swallow. If product is accidentally swallowed in quantities greater than would normally occur with a treatment gel, seek medical help or contact a Poison Control Center right away.
- Read directions carefully before using.

Dosage and Administration:

Shake well before use. This is a one minute or four minute fluoride gel for in-office patient use. It is normally used as a preventative caries treatment two times a year.

1. After thorough prophylaxsis, fill two single or one dual tray, one third full with gel. Air dry teeth and insert trays into the mouth.

2. Instruct patient to bite down lightly but firmly for one minute (80% effectiveness) or four minutes (100% effectiveness).

3. Remove trays. Instruct patient to expectorate any excess gel and not to eat or drink for at least 30 minutes.

Other Information:

Store at controlled room temperature 59° to 86°F (15°-30°C).

Protect from freezing.

Inactive Ingredients:

Citric Acid, FD&C Red #40, Flavor, Magnesium Aluminum Silicate, Phosphoric Acid, Polysorbate 20, Sodium Benzoate, Sodium Saccharin, Titanium Dioxide, Water, Xanthan Gum, Xylitol.